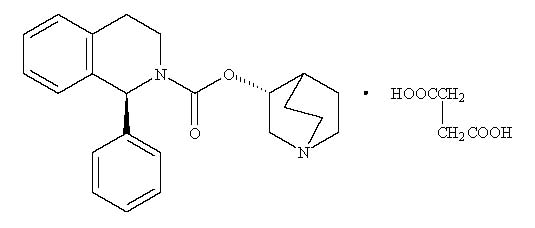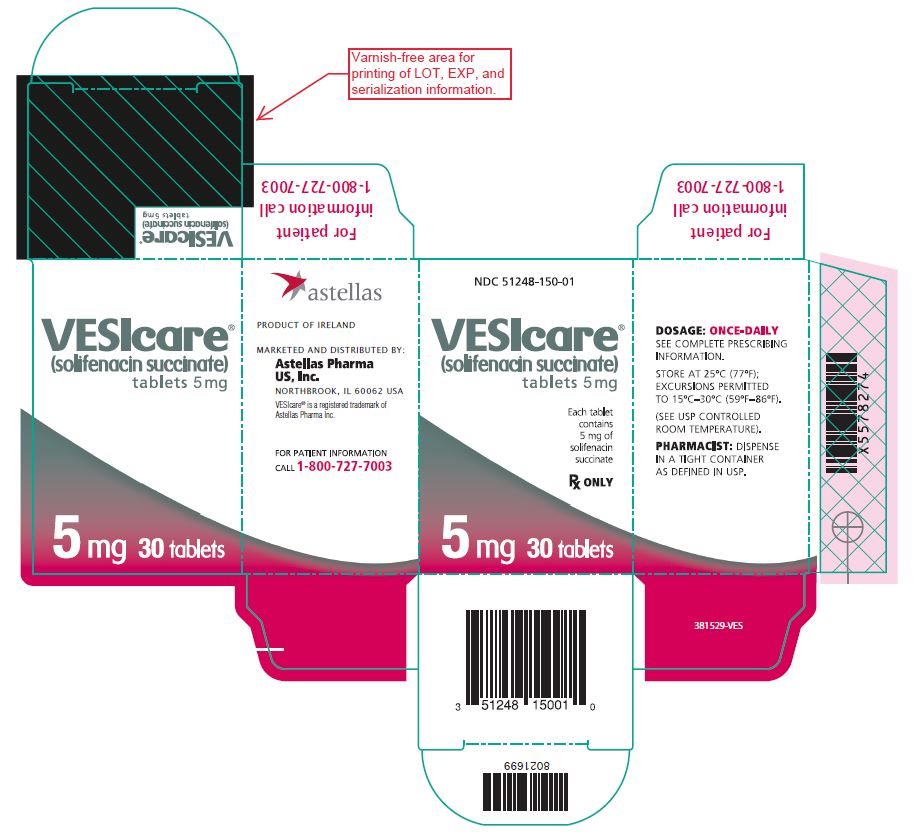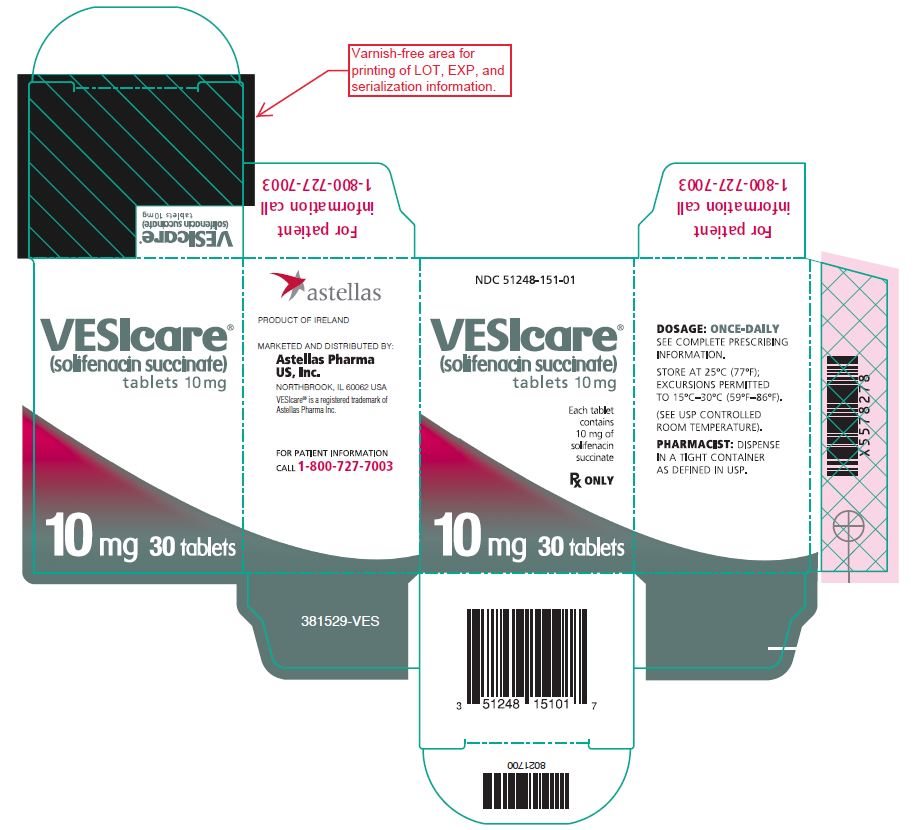 DRUG LABEL: VESIcare
NDC: 51248-150 | Form: TABLET, FILM COATED
Manufacturer: Astellas Pharma US, Inc.
Category: prescription | Type: HUMAN PRESCRIPTION DRUG LABEL
Date: 20221031

ACTIVE INGREDIENTS: SOLIFENACIN SUCCINATE 5 mg/1 1

HIGHLIGHTS OF PRESCRIBING INFORMATION

These highlights do not include all the information needed to use VESICARE safely and effectively. See full prescribing information for VESICARE.
VESICARE® (solifenacin succinate) tablets, for oral use
Initial U.S. Approval: 2004

1 INDICATIONS AND USAGE

VESIcare is a muscarinic antagonist indicated for the treatment of adults with overactive bladder with symptoms of urge urinary incontinence, urgency, and urinary frequency. (1)

2 DOSAGE AND ADMINISTRATION

- 5 mg tablet taken orally once daily, and if well tolerated may be increased to 10 mg once daily. (2.1)
- Do not exceed the 5 mg dose of VESIcare in patients with:
  - Severe renal impairment creatinine clearance < 30 mL/min/1.73 m^2. (2.2, 8.6)
  - Moderate hepatic impairment (Child-Pugh B). VESIcare is not recommended in patients with severe hepatic impairment (Child-Pugh C). (2.3, 8.7)
  - Concomitant use of strong CYP3A4 inhibitors. (2.4, 7.1)

3 DOSAGE FORMS AND STRENGTHS

Tablets: 5 mg and 10 mg. (3)

4 CONTRAINDICATIONS

- Urinary retention. (4, 5.2)
- Gastric retention. (4, 5.3)
- Uncontrolled narrow-angle glaucoma. (4, 5.5)
- Hypersensitivity to this product or any of its components. (4, 5.1, 6.2)

5 WARNINGS AND PRECAUTIONS

- Angioedema and Anaphylactic Reactions: Promptly discontinue VESIcare and provide appropriate therapy. (5.1)
- Urinary Retention: VESIcare is not recommended for use in patients with clinically significant bladder outlet obstruction. (5.2)
- Gastrointestinal Disorders: VESIcare is not recommended for use in patients with decreased gastrointestinal motility. (5.3)
- Central Nervous System Effects: Somnolence has been reported with VESIcare. Advise patients not to drive or operate heavy machinery until they know how VESIcare affects them. (5.4)
- Controlled Narrow-Angle Glaucoma: Use VESIcare with caution in patients being treated for narrow-angle glaucoma. (5.5)
- QT Prolongation in Patients at High Risk of QT Prolongation: VESIcare is not recommended for use in patients at high risk of QT prolongation, including patients with a known history of QT prolongation and patients taking medications known to prolong the QT interval. (5.6)

6 ADVERSE REACTIONS

The most common adverse reactions (> 4% in VESIcare-treated patients and > placebo-treated patients) were dry mouth and constipation at both 5 mg and 10 mg doses; and urinary tract infection and blurred vision at the 10 mg dose. (6.1)

To report SUSPECTED ADVERSE REACTIONS, contact Astellas Pharma US, Inc. at 1-800-727-7003 or FDA at 1-800-FDA-1088 or www.fda.gov/medwatch.

7 DRUG INTERACTIONS

CYP3A4 Inhibitors: Do not exceed the 5 mg dose of VESIcare with concomitant use of strong CYP3A4 inhibitors. (7.1)

FULL PRESCRIBING INFORMATION

1 INDICATIONS AND USAGE

VESIcare® is indicated for the treatment of adults with overactive bladder with symptoms of urge urinary incontinence, urgency, and urinary frequency.

2 DOSAGE AND ADMINISTRATION

2.1 Dosing Information

The recommended oral dose of VESIcare is 5 mg once daily. If the 5 mg dose is well tolerated, the dose may be increased to 10 mg once daily.

VESIcare should be taken with water and swallowed whole. VESIcare can be administered with or without food.

2.2 Dosing Recommendations in Patients with Renal Impairment

Do not exceed 5 mg once daily in patients with severe renal impairment (CLcr < 30 mL/min/1.73 m^2) [see Use in Specific Populations (8.6)].

2.3 Dosing Recommendations in Patients with Hepatic Impairment

Do not exceed 5 mg once daily in patients with moderate hepatic impairment (Child-Pugh B). Do not use VESIcare in patients with severe hepatic impairment (Child-Pugh C) [see Use in Specific Populations (8.7)].

2.4 Dosing Recommendations in Patients Taking CYP3A4 Inhibitors

Do not exceed 5 mg once daily when VESIcare is administered with strong CYP3A4 inhibitors such as ketoconazole [see Drug Interactions (7.1)].

3 DOSAGE FORMS AND STRENGTHS

Tablets:

- 5 mg: round, light yellow, debossed with 150
- 10 mg: round, light pink, debossed with 151

4 CONTRAINDICATIONS

VESIcare is contraindicated in patients:

- With urinary retention [see Warnings and Precautions (5.2)],
- With gastric retention [see Warnings and Precautions (5.3)],
- With uncontrolled narrow-angle glaucoma [see Warnings and Precautions (5.5)], and
- Who have demonstrated hypersensitivity to solifenacin succinate or the inactive ingredients in VESIcare. Reported adverse reactions have included anaphylaxis and angioedema [see Adverse Reactions (6.2)].

5 WARNINGS AND PRECAUTIONS

5.1 Angioedema and Anaphylactic Reactions

Angioedema of the face, lips, tongue, and/or larynx have been reported with solifenacin succinate. In some cases, angioedema occurred after the first dose, however, cases have been reported to occur hours after the first dose or after multiple doses. Anaphylactic reactions have also been reported in patients treated with solifenacin succinate. Angioedema associated with upper airway swelling and anaphylactic reactions may be life-threatening.

VESIcare is contraindicated in patients with a known or suspected hypersensitivity to solifenacin succinate [see Contraindications (4)]. If involvement of the tongue, hypopharynx, or larynx occurs, promptly discontinue VESIcare and provide appropriate therapy and/or measures necessary to ensure a patent airway.

5.2 Urinary Retention

The use of VESIcare, like other antimuscarinic drugs, in patients with clinically significant bladder outlet obstruction including patients with urinary retention, may result in further urinary retention and kidney injury. The use of VESIcare is not recommended in patients with clinically significant bladder outlet obstruction and is contraindicated in patients with urinary retention [see Contraindications (4)].

5.3 Gastrointestinal Disorders

The use of VESIcare, like other antimuscarinic drugs, in patients with conditions associated with decreased gastrointestinal motility may result in further decreased gastrointestinal motility. VESIcare is contraindicated in patients with gastric retention [see Contraindications (4)]. The use of VESIcare is not recommended in patients with conditions associated with decreased gastrointestinal motility.

5.4 Central Nervous System Effects

VESIcare is associated with antimuscarinic central nervous system (CNS) adverse reactions [see Adverse Reactions (6.2)]. A variety of CNS antimuscarinic adverse reactions have been reported, including headache, confusion, hallucinations, and somnolence. Monitor patients for signs of antimuscarinic CNS adverse reactions, particularly after beginning treatment or increasing the dose. Advise patients not to drive or operate heavy machinery until they know how VESIcare affects them. If a patient experiences antimuscarinic CNS adverse reactions, consider dose reduction or drug discontinuation.

5.5 Controlled Narrow-Angle Glaucoma

VESIcare should be used with caution in patients being treated for narrow-angle glaucoma [see Contraindications (4)].

5.6 QT Prolongation in Patients at High Risk of QT Prolongation

In a study of the effect of solifenacin succinate on the QT interval conducted in 76 healthy women [see Clinical Pharmacology (12.2)], solifenacin succinate 30 mg (three times the largest maximum recommended dose in adult patients) was associated with a mean increase in the Fridericia-corrected QT interval of 8 msec (90% CI, 4, 13). The QT prolonging effect appeared less with solifenacin succinate 10 mg than with solifenacin succinate 30 mg, and the effect of solifenacin succinate 30 mg did not appear as large as that of the positive control moxifloxacin at its therapeutic dose.

The use of VESIcare is not recommended in patients at high risk of QT prolongation, including patients with a known history of QT prolongation and patients who are taking medications known to prolong the QT interval.

6 ADVERSE REACTIONS

6.1 Clinical Trials Experience

Because clinical trials are conducted under widely varying conditions, adverse reaction rates observed in the clinical trials of a drug cannot be directly compared to rates in the clinical trials of another drug and may not reflect the rates observed in practice.

VESIcare has been evaluated for safety in 1811 adult patients in four randomized, placebo-controlled trials (Studies 1-4) [see Clinical Studies (14)]. Expected adverse reactions of antimuscarinic agents are dry mouth, constipation, blurred vision (accommodation abnormalities), urinary retention, and dry eyes. The incidence of dry mouth and constipation in patients treated with VESIcare was higher in the 10 mg dose group compared to the 5 mg dose group.

In the four 12-week double-blind clinical trials, severe fecal impaction, colonic obstruction, and intestinal obstruction were reported in one patient each, all in the VESIcare 10 mg group. Angioneurotic edema was reported in one patient taking VESIcare 5 mg. Compared to 12 weeks of treatment with VESIcare, the incidence and severity of adverse reactions were similar in patients who remained on drug for up to 12 months in Study 5 [see Clinical Studies (14)].

The most frequent adverse reaction leading to study discontinuation was dry mouth (1.5%). Table 1 lists the rates of identified adverse reactions, in the four randomized, placebo-controlled trials at an incidence greater than placebo and in 1% or more of patients treated with VESIcare 5 or 10 mg once daily for up to 12 weeks.

Table 1: Adverse Reactions Reported by ≥ 1% of Patients and Exceeding Placebo in Studies 1, 2, 3 and 4
 | Placebo (%) | VESIcare 5 mg (%) | VESIcare 10 mg (%)
Number of Patients | 1216 | 578 | 1233
GASTROINTESTINAL DISORDERS
Dry Mouth | 4.2 | 10.9 | 27.6
Constipation | 2.9 | 5.4 | 13.4
Nausea | 2.0 | 1.7 | 3.3
Dyspepsia | 1.0 | 1.4 | 3.9
Abdominal Pain Upper | 1.0 | 1.9 | 1.2
Vomiting NOS | 0.9 | 0.2 | 1.1
INFECTIONS AND INFESTATIONS
Urinary Tract Infection NOS | 2.8 | 2.8 | 4.8
Influenza | 1.3 | 2.2 | 0.9
Pharyngitis NOS | 1.0 | 0.3 | 1.1
NERVOUS SYSTEM DISORDERS
Dizziness | 1.8 | 1.9 | 1.8
EYE DISORDERS
Vision Blurred | 1.8 | 3.8 | 4.8
Dry Eyes NOS | 0.6 | 0.3 | 1.6
RENAL AND URINARY DISORDERS
Urinary Retention | 0.6 | 0 | 1.4
GENERAL DISORDERS AND ADMINISTRATION SITE CONDITIONS
Edema Lower Limb | 0.7 | 0.3 | 1.1
Fatigue | 1.1 | 1.0 | 2.1
PSYCHIATRIC DISORDERS
Depression NOS | 0.8 | 1.2 | 0.8
RESPIRATORY, THORACIC AND MEDIASTINAL DISORDERS
Cough | 0.2 | 0.2 | 1.1
VASCULAR DISORDERS
Hypertension NOS | 0.6 | 1.4 | 0.5

6.2 Postmarketing Experience

The following adverse reactions have been identified during post-approval use of solifenacin succinate in the U.S. and/or outside of the U.S. Because these reactions are reported voluntarily from a population of uncertain size, it is not always possible to reliably estimate their frequency or establish a causal relationship to drug exposure.

General disorders and administration site conditions: peripheral edema, hypersensitivity reactions (including angioedema with airway obstruction, rash, pruritus, urticaria, anaphylactic reaction);

Nervous system disorders: dizziness, headache, confusion, hallucinations, delirium, somnolence;

Cardiac disorders: QT prolongation, Torsade de Pointes, atrial fibrillation, tachycardia, palpitations;

Hepatobiliary disorders: liver disorders mostly characterized by abnormal liver function tests, AST (aspartate aminotransferase), ALT (alanine aminotransferase), GGT (gamma-glutamyl transferase);

Renal and urinary disorders: renal impairment, urinary retention;

Metabolism and nutrition disorders: decreased appetite, hyperkalemia;

Skin and subcutaneous tissue disorders: exfoliative dermatitis, erythema multiforme, dry skin;

Eye disorders: glaucoma;

Gastrointestinal disorders: gastroesophageal reflux disease, ileus, vomiting, abdominal pain, dysgeusia, sialadenitis;

Respiratory, thoracic and mediastinal disorders: dysphonia, nasal dryness;

Musculoskeletal and connective tissue disorders: muscular weakness.

7 DRUG INTERACTIONS

7.1 Strong CYP3A4 Inhibitors

Solifenacin is a substrate of CYP3A4. Concomitant use of ketoconazole, a strong CYP3A4 inhibitor, significantly increased the exposure of solifenacin [see Clinical Pharmacology (12.3)]. The dosage of VESIcare greater than 5 mg once daily is not recommended when concomitantly used with strong CYP3A4 inhibitors [see Dosage and Administration (2.4)].

8 USE IN SPECIFIC POPULATIONS

8.1 Pregnancy

Risk Summary

There are no studies with the use of solifenacin succinate in pregnant women to inform a drug-associated risk of major birth defects, miscarriages, or adverse maternal or fetal outcomes. No adverse developmental outcomes were observed in animal reproduction studies with oral administration of solifenacin succinate to pregnant mice during the period of organogenesis at a dose resulting in 1.2 times the systemic exposure at the maximum recommended human dose (MRHD) of 10 mg/day. However, administration of doses 3.6 times and greater than the MRHD during organogenesis produced maternal toxicity in the pregnant mice and resulted in developmental toxicity and reduced fetal body weights in offspring [see Data].

In the U.S. general population, the estimated background risk of major birth defects or miscarriage in clinically recognized pregnancies is 2-4% and 15-20%, respectively.

Data

Animal Data

Oral administration of ^14C-solifenacin succinate to pregnant mice resulted in the recovery of radiolabel in the fetus indicating that solifenacin-related product can cross the placental barrier. In pregnant mice, administration of solifenacin succinate at a dose of 250 mg/kg/day (7.9 times the systemic exposure at the MRHD of 10 mg), resulted in an increased incidence of cleft palate and increased maternal lethality. Administration of solifenacin succinate to pregnant mice during organogenesis at greater than or equal to 3.6 times (100 mg/kg/day and greater) the systemic exposure at the MRHD, resulted in reduced fetal body weights and reduced maternal body weight gain. No embryo-fetal toxicity or teratogenicity was observed in fetuses from pregnant mice treated with solifenacin succinate at a dose of 30 mg/kg/day (1.2 times the systemic exposure at the MRHD). Administration of solifenacin succinate to pregnant rats and rabbits at a dose of 50 mg/kg/day (< 1 times and 1.8 times the systemic exposure at the MRHD, respectively), resulted in no findings of embryo-fetal toxicity. Oral pre- and post-natal administration of solifenacin succinate at 100 mg/kg/day (3.6 times the systemic exposure at the MRHD) during the period of organogenesis through weaning, resulted in reduced peripartum and postnatal survival, reduced body weight gain by the pups, and delayed physical development (eye opening and vaginal patency). An increase in the percentage of male offspring was also observed in litters from offspring (F2 generation) exposed to maternal doses of 250 mg/kg/day. There were no effects on natural delivery in mice treated with 1.2 times (30 mg/kg/day) the expected systemic exposure at the MRHD.

8.2 Lactation

Risk Summary

There is no information on the presence of solifenacin in human milk, the effects on the breastfed child, or the effects on milk production. Solifenacin is present in mouse milk [see Data]. When a drug is present in animal milk, it is likely that the drug will be present in human milk. The developmental and health benefits of breastfeeding should be considered along with the mother’s clinical need for VESIcare and any potential adverse effects on the breastfed child from VESIcare or from the underlying maternal condition.

Data

Animal Data

Oral administration of ^14C-solifenacin succinate to lactating mice resulted in the recovery of radioactivity in maternal milk. Lactating female mice orally administered solifenacin succinate at a maternally toxic dose of 100 mg/kg/day (3.6 times the systemic exposure at the MRHD) had increased postpartum pup mortality, pups with reduced body weights, or delays in the onset of reflex and physical development. Pups from lactating dams orally administered solifenacin succinate at a dose of 30 mg/kg/day (1.2 times the systemic exposure at the MRHD) had no discernible adverse findings. The concentrations of solifenacin in animal milk does not necessarily predict the concentration of drug in human milk.

8.4 Pediatric Use

The safety and effectiveness of VESIcare Tablets have not been established in pediatric patients.

8.5 Geriatric Use

In placebo-controlled clinical studies, similar safety and effectiveness were observed between geriatric patients (623 patients ≥ 65 years and 189 patients ≥ 75 years) and younger adult patients (1188 patients < 65 years) treated with VESIcare [see Clinical Pharmacology (12.3)].

8.6 Renal Impairment

Solifenacin plasma concentrations are greater in patients with severe renal impairment compared to subjects with normal renal function [see Clinical Pharmacology (12.3)]. Because increased solifenacin plasma concentrations increase the risk of antimuscarinic adverse reactions, the maximum recommended dose of VESIcare in patients with severe renal impairment (CLcr < 30 mL/min/1.73 m^2) is 5 mg once daily [see Dosage and Administration (2.2)]. The recommended dose in patients with mild or moderate renal impairment is the same as in patients with normal renal function.

8.7 Hepatic Impairment

Solifenacin plasma concentrations are greater in patients with moderate hepatic impairment compared to subjects with normal hepatic function [see Clinical Pharmacology (12.3)]. Because increased solifenacin plasma concentrations increase the risk of antimuscarinic adverse reactions, the maximum recommended dose of VESIcare in patients with moderate hepatic impairment (Child-Pugh B) is 5 mg once daily [see Dosage and Administration (2.3)] and VESIcare is not recommended for use in patients with severe hepatic impairment (Child-Pugh C).

8.8 Gender

The pharmacokinetics of solifenacin is not significantly influenced by gender.

10 OVERDOSAGE

Overdosage with VESIcare can potentially result in severe antimuscarinic effects and should be treated accordingly. The highest dose ingested in an accidental overdose of solifenacin succinate was 280 mg (28 times the maximum dosage) in a 5-hour period. This case was associated with mental status changes. Some cases reported a decrease in the level of consciousness.

Intolerable antimuscarinic adverse reactions (fixed and dilated pupils, blurred vision, failure of heel-to-toe exam, tremors, and dry skin) occurred on day 3 in normal volunteers taking 50 mg daily (5 times the maximum recommended therapeutic dose) and resolved within 7 days following discontinuation of drug.

In the event of overdose with VESIcare, treat with gastric lavage and appropriate supportive measures. ECG monitoring is also recommended.

11 DESCRIPTION

VESIcare (solifenacin succinate) is a muscarinic receptor antagonist. Chemically, solifenacin succinate is a butanedioic acid compound with (1S)-(3R)-1-azabicyclo[2.2.2]oct-3-yl 3,4-dihydro-1-phenyl-2(1H)-iso-quinolinecarboxylate (1:1) having an empirical formula of C23H26N2O2•C4H6O4, and a molecular weight of 480.55. The structural formula of solifenacin succinate is:

Solifenacin succinate is a white to pale-yellowish-white crystal or crystalline powder. It is freely soluble at room temperature in water, glacial acetic acid, dimethyl sulfoxide, and methanol.

Each VESIcare tablet contains 5 or 10 mg of solifenacin succinate and is for oral administration. In addition to the active ingredient solifenacin succinate, each VESIcare tablet also contains the following inactive ingredients: lactose monohydrate, corn starch, hypromellose 2910, magnesium stearate, talc, polyethylene glycol 8000 and titanium dioxide with yellow ferric oxide (5 mg VESIcare tablet) or red ferric oxide (10 mg VESIcare tablet).

12 CLINICAL PHARMACOLOGY

12.1 Mechanism of Action

Solifenacin is a competitive muscarinic receptor antagonist. Muscarinic receptors play an important role in several major cholinergically mediated functions, including contractions of urinary bladder smooth muscle.

12.2 Pharmacodynamics

Cardiac Electrophysiology

The effect of 10 mg and 30 mg solifenacin succinate (three times the maximum recommended dose) on the QT interval was evaluated at the time of peak plasma concentration of solifenacin in a multi-dose, randomized, double-blind, placebo and positive-controlled (moxifloxacin 400 mg) trial [see Warnings and Precautions (5.6)]. After receiving placebo and moxifloxacin sequentially, subjects were randomized to one of two treatment groups. One group (n=51) completed 3 additional sequential periods of dosing with solifenacin succinate 10, 20, and 30 mg while the second group (n=25) in parallel completed a sequence of placebo and moxifloxacin. Study subjects were female volunteers aged 19 to 79 years. The 30 mg dose of solifenacin succinate (three times the highest recommended dose) was chosen for use in this study because this dose results in a solifenacin exposure that covers those observed upon coadministration of 10 mg VESIcare with strong CYP3A4 inhibitors (e.g., ketoconazole, 400 mg). Due to the sequential dose escalating nature of the study, baseline ECG measurements were separated from the final QT assessment (of the 30 mg dose level) by 33 days.

The median difference from baseline in heart rate associated with the 10 and 30 mg doses of solifenacin succinate compared to placebo was -2 and 0 beats/minute, respectively. Because a significant period effect on QTc was observed, the QTc effects were analyzed utilizing the parallel placebo control arm rather than the pre-specified intra-patient analysis. Representative results are shown in Table 2.

Table 2: QTc changes in msec (90% CI) from baseline at Tmax (relative to placebo) [Results displayed are those derived from the parallel design portion of the study and represent the comparison of Group 1 to time-matched placebo effects in Group 2.]
Drug/Dose | Fridericia method (using mean difference)
Solifenacin succinate 10 mg | 2 (-3, 6)
Solifenacin succinate 30 mg | 8 (4, 13)

Moxifloxacin was included as a positive control in this study and, given the length of the study, its effect on the QT interval was evaluated in 3 different sessions. The placebo-subtracted mean changes (90% CI) in QTcF for moxifloxacin in the three sessions were 11 (7, 14), 12 (8, 17), and 16 (12, 21), respectively.

The QT interval prolonging effect of the highest solifenacin succinate dose (three times the maximum therapeutic dose) studied was not as large as that of the positive control moxifloxacin at its recommended dose. However, the confidence intervals overlapped, and this study was not designed to draw direct statistical conclusions between the drugs or the dose levels.

12.3 Pharmacokinetics

Absorption

After oral administration of VESIcare in healthy volunteers, peak plasma concentrations (Cmax) of solifenacin were reached within 3 to 8 hours after administration and, at steady-state, ranged from 32.3 to 62.9 ng/mL for the 5 and 10 mg VESIcare tablets, respectively. The absolute bioavailability of solifenacin is approximately 90%, with plasma concentrations of solifenacin proportional to the dose administered.

Effect of Food
VESIcare may be administered without regard to meals. A single 10 mg dose administration of VESIcare with food increased Cmax and AUC of solifenacin by 4% and 3%, respectively.

Distribution

Solifenacin is approximately 98% (in vivo) bound to human plasma proteins, principally to α1-acid glycoprotein. Solifenacin is highly distributed to non-CNS tissues, having a mean steady-state volume of distribution of 600 L.

Elimination

The elimination half-life (t1/2) of solifenacin following chronic dosing is approximately 45-68 hours.

Metabolism
Solifenacin is extensively metabolized in the liver. The primary pathway for elimination is by way of CYP3A4; however, alternate metabolic pathways exist. The primary metabolic routes of solifenacin are through N-oxidation of the quinuclidin ring and 4R-hydroxylation of the tetrahydroisoquinoline ring. One pharmacologically active metabolite (4R-hydroxy solifenacin), occurring at low concentrations and unlikely to contribute significantly to clinical activity, and three pharmacologically inactive metabolites (N-glucuronide and the N-oxide and 4R-hydroxy-N-oxide of solifenacin) have been found in human plasma after oral dosing.
  Excretion
Following the administration of 10 mg of ^14C-solifenacin succinate to healthy volunteers, 69% of the radioactivity was recovered in the urine and 23% in the feces over 26 days. Less than 15% (as mean value) of the dose was recovered in the urine as intact solifenacin. The major metabolites identified in urine were N-oxide of solifenacin, 4R-hydroxy solifenacin, and 4R-hydroxy-N-oxide of solifenacin and, in feces, 4R-hydroxy solifenacin.

Specific Populations

Geriatric Patients
Multiple dose studies of VESIcare in geriatric volunteers (65 to 80 years) showed that Cmax, AUC and t1/2 values of solifenacin were 20-25% higher compared to the younger adult volunteers (18 to 55 years). [See Use in Specific Populations (8.5)].
  Patients with Renal Impairment
In studies with solifenacin succinate 10 mg, there was a 2.1-fold increase in AUC and a 1.6-fold increase in t1/2 of solifenacin in patients with severe renal impairment compared to subjects with normal renal function [see Use in Specific Populations (8.6)].
  Patients with Hepatic Impairment
In studies with solifenacin succinate 10 mg, there was a 2-fold increase in the t1/2 and a 35% increase in AUC of solifenacin in patients with moderate hepatic impairment compared to subjects with normal hepatic function [see Use in Specific Populations (8.7)]. VESIcare has not been studied in patients with severe hepatic impairment.

Drug Interaction Studies

Strong CYP3A4 Inhibitors
In a crossover study, following blockade of CYP3A4 by coadministration of the strong CYP3A4 inhibitor, ketoconazole 400 mg once daily for 21 days, the mean Cmax and AUC of solifenacin increased by 1.5 and 2.7-fold, respectively [see Dosage and Administration (2.4) and Drug Interactions (7.1)].
  CYP3A4 Inducers
Because solifenacin is a substrate of CYP3A4, inducers of CYP3A4 may decrease the concentration of solifenacin.
  Warfarin
In a crossover study, subjects received a single oral dose of warfarin 25 mg on the 10th day of dosing with either solifenacin succinate 10 mg or matching placebo once daily for 16 days. For R-warfarin, when it was coadministered with solifenacin succinate, the mean Cmax increased by 3% and AUC decreased by 2%. For S-warfarin, when it was coadministered with solifenacin succinate, the mean Cmax and AUC increased by 5% and 1%, respectively.
  Oral Contraceptives
In a crossover study, subjects received 2 cycles of 21 days of oral contraceptives containing 30 ug ethinyl estradiol and 150 ug levonorgestrel. During the second cycle, subjects received additional solifenacin succinate 10 mg or matching placebo once daily for 10 days starting from the 12th day of receipt of oral contraceptives. For ethinyl estradiol, when it was administered with solifenacin succinate, the mean Cmax and AUC increased by 2% and 3%, respectively. For levonorgestrel, when it was administered with solifenacin succinate, the mean Cmax and AUC decreased by 1%.
  Digoxin
In a crossover study, subjects received digoxin (loading dose of 0.25 mg on day 1, followed by 0.125 mg from days 2 to 8) for 8 days. Consecutively, they received solifenacin succinate 10 mg or matching placebo with digoxin 0.125 mg for an additional 10 days. When digoxin was coadministered with solifenacin succinate, the mean Cmax and AUC increased by 13% and 4%, respectively.
  Drugs Metabolized by Cytochrome P450 Enzymes
In vitro studies demonstrated that, at therapeutic concentrations, solifenacin does not inhibit CYP1A1/2, 2C9, 2C19, 2D6, or 3A4 derived from human liver microsomes.

13 NONCLINICAL TOXICOLOGY

13.1 Carcinogenesis, Mutagenesis, Impairment of Fertility

No increase in tumors was found following the administration of solifenacin succinate to male and female mice for 104 weeks at doses up to 200 mg/kg/day (5 and 9 times, respectively, of the exposure at the maximum recommended human dose [MRHD] of 10 mg), and male and female rats for 104 weeks at doses up to 20 and 15 mg/kg/day, respectively (< 1 times the exposure at the MRHD).

Solifenacin succinate was not mutagenic in the in vitro Salmonella typhimurium or Escherichia coli microbial mutagenicity test or chromosomal aberration test in human peripheral blood lymphocytes with or without metabolic activation or in the in vivo micronucleus test in rats.

Solifenacin succinate had no effect on reproductive function, fertility, or early embryonic development of the fetus in male and female mice treated with 250 mg/kg/day (13 times the exposure at the MRHD) of solifenacin succinate, and in male rats treated with 50 mg/kg/day (< 1 times the exposure at the MRHD) and female rats treated with 100 mg/kg/day (1.7 times the exposure at the MRHD) of solifenacin succinate.

13.2 Animal Toxicology and/or Pharmacology

Juvenile Animal Toxicology Data

Dose-related increased mortality without preceding clinical signs occurred in juvenile mice treated before weaning for a duration of 12 weeks, from day 10 after birth, with doses that achieved a pharmacological effect. Animals dosed from postnatal day 10 onwards had higher mortality compared to the mortality in adult mice. No increased frequency in mortality was observed in juvenile mice that were treated after weaning for a duration of 4 weeks, from day 21 after birth onwards. Plasma exposure at postnatal day 10 was higher than in adult mice; the systemic exposure at postnatal day 21 was comparable to the systemic exposure in adult mice.

14 CLINICAL STUDIES

VESIcare was evaluated in four twelve-week, double-blind, randomized, placebo-controlled, parallel group, multicenter clinical trials for the treatment of overactive bladder in adult patients having symptoms of urinary frequency, urgency, and/or urge or mixed incontinence (with a predominance of urge). Entry criteria required that patients have symptoms of overactive bladder for ≥ 3 months duration. These studies involved 3027 patients (1811 on VESIcare and 1216 on placebo), and approximately 90% of these patients completed the 12-week studies. Two of the four studies evaluated the 5 and 10 mg VESIcare doses (Studies 1 and 2) and the other two evaluated only the 10 mg dose (Studies 3 and 4). All patients completing the 12-week studies were eligible to enter an open-label, long-term extension study (Study 5) and 81% of patients enrolling completed the additional 40-week treatment period. The majority of patients were Caucasian (93%) and female (80%) with a mean age of 58 years.

The primary endpoint in all four trials was the mean change from baseline to 12 weeks in number of micturitions/24 hours. Secondary endpoints included mean change from baseline to 12 weeks in number of incontinence episodes/24 hours, and mean volume voided per micturition.

The efficacy of VESIcare was similar across patient age groups and gender. The mean reduction in the number of micturitions per 24 hours was significantly greater with VESIcare 5 mg (2.3; p < 0.001) and VESIcare 10 mg (2.7; p < 0.001) compared to placebo (1.4). The mean reduction in the number of incontinence episodes per 24 hours was significantly greater with VESIcare 5 mg (1.5; p < 0.001) and VESIcare 10 mg (1.8; p < 0.001) treatment groups compared to the placebo treatment group (1.1). The mean increase in the volume voided per micturition was significantly greater with VESIcare 5 mg (32.3 mL; p < 0.001) and VESIcare 10 mg (42.5 mL; p < 0.001) compared with placebo (8.5 mL).

The results for the primary and secondary endpoints in the four individual 12-week clinical studies of VESIcare are reported in Tables 3 through 6.

Table 3: Mean Changes from Baseline to Week 12 in Efficacy Endpoints in Study 1
Parameter | Placebo (N=253) Mean (SE) | VESIcare 5 mg (N=266) Mean (SE) | VESIcare 10 mg (N=264) Mean (SE)
Urinary Frequency (Number of Micturitions/24 hours) [Primary endpoint]
Baseline; Reduction; P value vs. placebo | 12.2 (0.26); 1.2 (0.21) | 12.1 (0.24); 2.2 (0.18); < 0.001 | 12.3 (0.24); 2.6 (0.20); < 0.001
Number of Incontinence Episodes/24 hours [Secondary endpoint]
Baseline; Reduction; P value vs. placebo | 2.7 (0.23); 0.8 (0.18) | 2.6 (0.22); 1.4 (0.15); < 0.01 | 2.6 (0.23); 1.5 (0.18); < 0.01
Volume Voided per Micturition [mL]
Baseline; Increase; P value vs. placebo | 143.8 (3.37); 7.4 (2.28) | 149.6 (3.35); 32.9 (2.92); < 0.001 | 147.2 (3.15); 39.2 (3.11); < 0.001

Table 4: Mean Changes from Baseline to Week 12 in Efficacy Endpoints in Study 2
Parameter | Placebo (N=281) Mean (SE) | VESIcare 5 mg (N=286) Mean (SE) | VESIcare 10 mg (N=290) Mean (SE)
Urinary Frequency (Number of Micturitions/24 hours) [Primary endpoint]
Baseline; Reduction; P value vs. placebo | 12.3 (0.23); 1.7 (0.19) | 12.1 (0.23); 2.4 (0.17); < 0.001 | 12.1 (0.21); 2.9 (0.18); < 0.001
Number of Incontinence Episodes/24 hours [Secondary endpoint]
Baseline; Reduction; P value vs. placebo | 3.2 (0.24); 1.3 (0.19) | 2.6 (0.18); 1.6 (0.16); < 0.01 | 2.8 (0.20); 1.6 (0.18); 0.016
Volume Voided per Micturition [mL]
Baseline; Increase; P value vs. placebo | 147.2 (3.18); 11.3 (2.52) | 148.5 (3.16); 31.8 (2.94); < 0.001 | 145.9 (3.42); 36.6 (3.04); < 0.001

Table 5: Mean Changes from Baseline to Week 12 in Efficacy Endpoints in Study 3
Parameter | Placebo (N=309) Mean (SE) | VESIcare 10 mg (N=306) Mean (SE)
Urinary Frequency (Number of Micturitions/24 hours) [Primary endpoint]
Baseline; Reduction; P value vs. placebo | 11.5 (0.18); 1.5 (0.15) | 11.7 (0.18); 3.0 (0.15); < 0.001
Number of Incontinence Episodes/24 hours [Secondary endpoint]
Baseline; Reduction; P value vs. placebo | 3.0 (0.20); 1.1 (0.16) | 3.1 (0.22); 2.0 (0.19); < 0.001
Volume Voided per Micturition [mL]
Baseline; Increase; P value vs. placebo | 190.3 (5.48); 2.7 (3.15) | 183.5 (4.97); 47.2 (3.79); < 0.001

Table 6: Mean Changes from Baseline to Week 12 in Efficacy Endpoints in Study 4
Parameter | Placebo (N=295) Mean (SE) | VESIcare 10 mg (N=298) Mean (SE)
Urinary Frequency (Number of Micturitions/24 hours) [Primary endpoint]
Baseline; Reduction; P value vs. placebo | 11.8 (0.18); 1.3 (0.16) | 11.5 (0.18); 2.4 (0.15); < 0.001
Number of Incontinence Episodes/24 hours [Secondary endpoint]
Baseline; Reduction; P value vs. placebo | 2.9 (0.18); 1.2 (0.15) | 2.9 (0.17); 2.0 (0.15); < 0.001
Volume Voided per Micturition [mL]
Baseline; Increase; P value vs. placebo | 175.7 (4.44); 13.0 (3.45) | 174.1 (4.15); 46.4 (3.73); < 0.001

16 HOW SUPPLIED/STORAGE AND HANDLING

VESIcare is supplied as round, film-coated tablets, available in bottles as follows:

Each 5 mg tablet is light yellow and debossed with a logo and “150” and is available as follows:

Bottle of 30 NDC 51248-150-01

Each 10 mg tablet is light pink and debossed with a logo and “151” and is available as follows:

Bottle of 30 NDC 51248-151-01
Bottle of 90 NDC 51248-151-03

Store at 25°C (77°F) with excursions permitted from 15°C to 30°C (59°F to 86°F) [see USP Controlled Room Temperature].

17 PATIENT COUNSELING INFORMATION

Advise the patient to read the FDA-approved patient labeling (Patient Information).

Angioedema and Anaphylactic Reactions

Inform patients that angioedema and anaphylactic reactions have been reported in patients treated with VESIcare. Angioedema and anaphylactic reactions may be life-threatening. Advise patients to promptly discontinue VESIcare therapy and seek immediate attention if they experience edema of the tongue or laryngopharynx, or difficulty breathing [see Contraindications (4) and Warnings and Precautions (5.1)].

Urinary Retention

Inform patients that VESIcare may cause urinary retention in patients with conditions associated with bladder outlet obstruction [see Warnings and Precautions (5.2)].

Gastrointestinal Disorders

Inform patients that VESIcare may cause further decrease in gastrointestinal motility in patients with conditions associated with decreased gastrointestinal motility. VESIcare has been associated with constipation and dry mouth. Advise patients to contact their health care providers if they experience severe abdominal pain or become constipated for 3 or more days [see Warnings and Precautions (5.3)].

Central Nervous System Effects

Because VESIcare, like other antimuscarinic agents, may cause central nervous system effects or blurred vision, advise patients to exercise caution in decisions to engage in potentially dangerous activities until the drug’s effect on the patient has been determined [see Warnings and Precautions (5.4)].

Narrow-Angle Glaucoma

Inform patients that VESIcare, like other antimuscarinics, may cause worsening of the glaucoma condition in patients with narrow-angle glaucoma [see Warnings and Precautions (5.5)].

Dry Skin

Inform patients that VESIcare, like other antimuscarinics, may cause dry skin due to decreased sweating. Heat prostration due to decreased sweating can occur when VESIcare is used in a hot environment [see Adverse Reactions (6.2)].

Marketed and Distributed by:
Astellas Pharma US, Inc.
Northbrook, IL 60062

VESIcare is a registered trademark of Astellas Pharma Inc.

© 2004 – 2022 Astellas Pharma US, Inc.

361078-VES

Patient Information

VESIcare® (VES-ih-care)

(solifenacin succinate)

Tablet

Read the Patient Information that comes with VESIcare® before you start taking it and each time you get a refill. There may be new information. This leaflet does not take the place of talking with your doctor about your medical condition or treatment.

What is VESIcare?

VESIcare is a prescription medicine for adults used to treat the following symptoms due to a condition called overactive bladder:

- Urge urinary incontinence: a strong need to urinate with leaking or wetting accidents
- Urgency: a strong need to urinate right away
- Frequency: urinating often

VESIcare 5 mg and 10 mg tablets are not approved for use in children.

Who should not take VESIcare?

Do not take VESIcare if you:

- are not able to empty your bladder (urinary retention)
- have delayed or slow emptying of your stomach (gastric retention)
- have an eye problem called “uncontrolled narrow-angle glaucoma”
- are allergic to solifenacin succinate or any of the ingredients in VESIcare. See the end of this leaflet for a complete list of ingredients.

What should I tell my doctor before taking VESIcare?

Before you take VESIcare, tell your doctor if you:

- have any stomach or intestinal problems or problems with constipation
- have trouble emptying your bladder or you have a weak urine stream
- have an eye problem called “narrow-angle glaucoma”
- have liver problems
- have kidney problems
- have a rare heart problem called “QT prolongation”
- are pregnant or plan to become pregnant. It is not known if VESIcare will harm your unborn baby. Talk to your doctor if you are pregnant or plan to become pregnant.
- are breastfeeding or plan to breastfeed. It is not known if VESIcare passes into your breast milk. You and your doctor should decide if you will take VESIcare or breastfeed.

Tell your doctor about all the medicines you take, including prescription and nonprescription medicines, vitamins, and herbal supplements. VESIcare may affect the way other medicines work, and other medicines may affect how VESIcare works.

How should I take VESIcare?

- Take VESIcare exactly as your doctor tells you to take it.
- You should take 1 VESIcare tablet 1 time a day.
- You should take VESIcare with water and swallow the tablet whole.
- You can take VESIcare with or without food.
- If you miss a dose of VESIcare, begin taking VESIcare again the next day. Do not take 2 doses of VESIcare the same day.
- If you take too much VESIcare, call your doctor or go to the nearest hospital emergency room
  right away.

What should I avoid while taking VESIcare?

VESIcare can cause blurred vision or drowsiness. Do not drive or operate heavy machinery until you know how VESIcare affects you.

What are the possible side effects of VESIcare?

VESIcare may cause serious side effects including:

- Serious allergic reaction. Stop taking VESIcare and get medical help right away if you have:
  - hives, skin rash or swelling
  - severe itching
  - swelling of your face, mouth or tongue
  - trouble breathing

The most common side effects of VESIcare include:

- dry mouth
- constipation. Call your doctor if you get severe stomach area (abdominal) pain or become constipated for 3 or more days.
- urinary tract infection
- blurred vision

Other side effects have been observed with anticholinergic drugs such as VESIcare and may include:

- dry skin due to decreased sweating. Heat exhaustion or heat stroke can happen due to decreased sweating when VESIcare is used in hot environments. Symptoms may include:
  - decreased sweating
  - dizziness
  - tiredness
  - nausea
  - increase in body temperature

Tell your doctor if you have any side effect that bothers you or that does not go away.

These are not all the possible side effects of VESIcare. For more information, ask your doctor or pharmacist.

Call your doctor for medical advice about side effects. You may report side effects to the FDA at 1-800-FDA-1088.

How should I store VESIcare?

- Store VESIcare between 59°F to 86°F (15°C to 30°C). Keep the bottle closed.
- Safely throw away medicine that is out of date or no longer needed.

Keep VESIcare and all medicines out of the reach of children.

General information about the safe and effective use of VESIcare

Medicines are sometimes prescribed for purposes other than those listed in Patient Information leaflets. Do not use VESIcare for a condition for which it was not prescribed. Do not give VESIcare to other people, even if they have the same symptoms you have. It may harm them.

This leaflet summarizes the most important information about VESIcare. If you would like more information, talk with your doctor. You can ask your doctor or pharmacist for information about VESIcare that is written for health professionals.

What are the ingredients in VESIcare?

Active ingredient: solifenacin succinate

Inactive ingredients: lactose monohydrate, corn starch, hypromellose 2910, magnesium stearate, talc, polyethylene glycol 8000 and titanium dioxide with yellow ferric oxide (5 mg VESIcare tablet) or red ferric oxide (10 mg VESIcare tablet)

What is overactive bladder?

Overactive bladder occurs when you cannot control your bladder contractions. When these muscle contractions happen too often or cannot be controlled you can get symptoms of overactive bladder, which are urinary frequency, urinary urgency, and urinary incontinence (leakage).
Marketed and Distributed by:

Astellas Pharma US, Inc.

Northbrook, Illinois 60062
VESIcare is a registered trademark of Astellas Pharma Inc.
© 2004 – 2022 Astellas Pharma US, Inc.
For more information, call 1-800-727-7003.
361078-VES

This Patient Information has been approved by the U.S. Food and Drug Administration. Revised: 10/2022

PRINCIPAL DISPLAY PANEL - 5 mg Carton

NDC 51248-150-01

VESIcare®
(solifenacin succinate)
tablets 5 mg

Each tablet contains 5 mg of solifenacin succinate

Rx ONLY

5 mg 30 tablets

PRINCIPAL DISPLAY PANEL – 10 mg Carton

NDC 51248-151-01

VESIcare®
(solifenacin succinate)
tablets 10 mg

Each tablet contains 10 mg of solifenacin succinate

Rx ONLY

10 mg 30 tablets